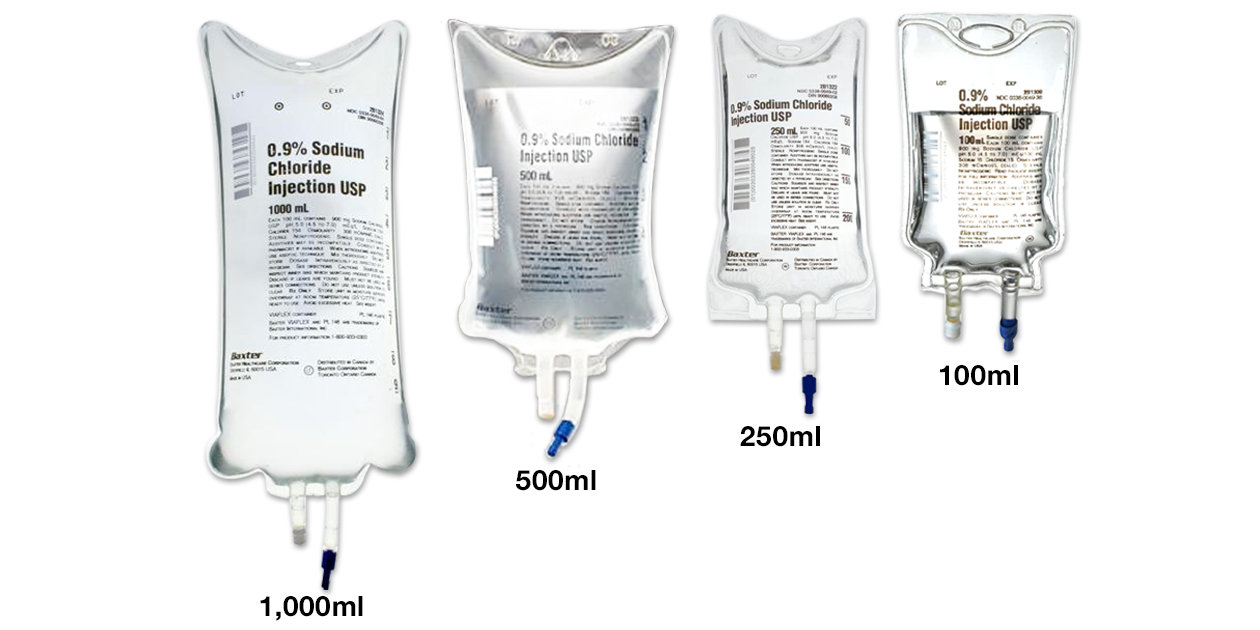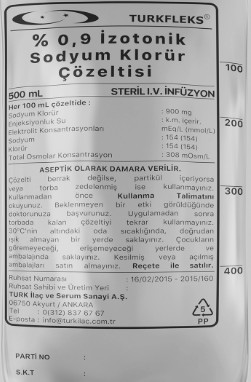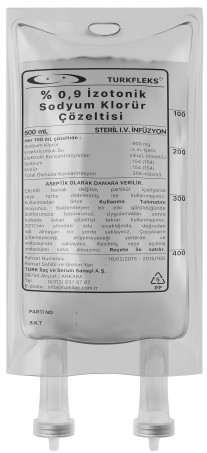 DRUG LABEL: Turkfleks %0.9 Sodium Chloride
NDC: 85160-200 | Form: INJECTION, SOLUTION
Manufacturer: TURK ILAC VE SERUM SANAYI ANONIM SIRKETI
Category: prescription | Type: HUMAN PRESCRIPTION DRUG LABEL
Date: 20250328

ACTIVE INGREDIENTS: CHLORIDE ION 0.9 g/100 mL

DESCRIPTION

Turkfleks %0.9 Sodium Chloride solution

Active substance: Each 100 ml solution contains 0.9 g sodium chloride. Excipients: Injection water

The osmolarity of the solution is 308 mOsmol/l.

Ion concentrations of the solution:

- sodium: 154 mEq/L

- chloride: 154 mEq/L

Sterile solution for intravenous infusion

CLINICAL PHARMACOLOGY

Therapeutic indications

TURKFLEKS %0.9 ISOTONIC SODIUM CHLORIDE is indicated in the following cases: - In the treatment of isotonic extracellular dehydration - In the treatment of sodium losses - As a diluent solution for drugs with which it is compatible in parenteral applications.

Dosage and method of administration

Dosage / frequency and duration of administration:

The dose to be administered should be determined by the physician for each patient based on the patient's age, body weight, clinical condition, and especially the patient's hydration status. Serum electrolyte concentrations should be carefully monitored during treatment. In general, in the treatment of isotonic extracellular dehydration and sodium losses, unless otherwise recommended by the physician, it is recommended at a dose of 500 - 3000 ml per 24 hours for adults, adolescents and the elderly, and 20 - 100 ml/kg per 24 hours for infants and children.

Method of administration:

Application is made intravenously through peripheral or central veins with sterile apyrogen sets. For details on administration, see also section 6.6.

Additional information regarding special populations:

Renal/Liver failure: Since there is no study specifically conducted for this population, there is no specific dosage recommendation for this patient group.

Pediatric population:

The dose and infusion rate to be administered are adjusted by the physician according to the patient's weight, clinical and biological status, and concomitant therapy, as in adults. In this population, a dose of 20 - 100 ml/kg per 24 hours is generally recommended.

Geriatric population: The dose and infusion rate to be administered are adjusted by the physician according to the patient's weight, clinical and biological status, and concomitant therapy, as in adults.

CONTRAINDICATIONS

The solution is contraindicated in patients with hypernatremia or hyperchloremia. It should also not be used in cases where sodium or chloride administration is clinically harmful.

WARNINGS AND PRECAUTIONS

Administration of intravenous solutions may lead to fluid and/or solute overload, which may cause dilution of serum electrolyte concentration, overhydration, congestive states, or pulmonary edema. The risk of dilution is inversely proportional to the electrolyte concentration. The risk of developing congestive states that may lead to peripheral and pulmonary edema is directly proportional to the electrolyte concentration in the solution. The solution contains 154 mmol/l sodium (Na+) and 154 mmol/l chloride (Cl-); its osmolarity is approximately 308 mOsm/l, and its pH is 5.5 (4.5 - 7.0).

Careful clinical monitoring is required at the beginning of all intravenous infusions. Applications should be carried out under regular and careful observation. Clinical and biological parameters, especially serum electrolyte levels, should be monitored. Sodium retention may be observed in premature or full-term newborn babies, since their renal functions are not yet fully developed. Therefore, repeated sodium chloride infusions should be given to newborn babies only after serum sodium levels have been determined. Solutions containing sodium should be used with caution in cases of hypertension, heart failure, peripheral or pulmonary edema or impaired renal function, in cases of preeclampsia, in cases of aldosteronism, or in other conditions and treatments that cause sodium retention (e.g., corticosteroid therapy).

Pseudohyponatremia is a condition in which plasma sodium is falsely low when measured by conventional methods, even though it is not actually low. It can occur when large molecules are in abnormally high concentrations and the plasma water ratio is abnormally low as a result. This condition, which can be seen in hyperlipemia and hyperproteinemia, has also been reported to be seen in patients with diabetes mellitus. Real values can be obtained by evaluating the concentration according to the plasma water ratio. Excessive application of potassium-free solutions can lead to a significant hypokalemia. Serum potassium levels should be maintained at normal levels and potassium should be added to the treatment if necessary. In order to minimize the risk of incompatibility with any other drug added to the solution, the final mixture to be infused should be checked for any turbidity or precipitation immediately after mixing, before administration and at certain intervals during administration.

If the application is to be made with a controlled infusion pump, care should be taken to ensure that the pump is stopped before the bag is completely emptied, otherwise air embolism may occur. The solution is administered intravenously through sterile sets. It is recommended that sets used for intravenous administration be changed every 24 hours. It should only be used if the solution is clear and the bag is intact and not leaking.

Laboratory tests: In long-term parenteral administration or when the patient's condition requires, clinical evaluation and periodic laboratory tests should be performed to monitor changes in the patient's fluid balance, electrolyte concentrations, and acid-base balance. When significant deviations from normal values are observed, these values should be normalized with alternative solutions. Warnings and precautions regarding pediatric use: Fluid and electrolyte balance in neonates or very young infants can be affected by even the administration of very small amounts of fluid. Care should be exercised in the treatment of neonates, especially preterm neonates, whose renal functions are not yet fully developed and whose ability to excrete solutes with fluids is limited. Fluid intake, urine output, and serum electrolyte levels should be closely monitored.

Warnings and precautions regarding use in the elderly: In general, the dose should be selected carefully in elderly patients. Considering that the liver, kidney or cardiac functions may be reduced in the elderly, other drugs may be used together or there may be diseases other than the condition being treated, it is generally recommended to start treatment with doses at the bottom of the dosage range.

OTHER SAFETY INFORMATION

Interactions with other medical products and other forms of interaction Some drugs or solutions added to the solution may be incompatible. As with all parenteral solutions, compatibility with additional drugs should be evaluated by the physician before use. If other substances are to be added to the solution, aseptic technique should be used and shaken until mixed. After adding the drugs to TURKFLEKS %0.9 ISOTONIC SODIUM CHLORIDE, it should be ensured that there is no color change, insoluble particles and crystallization. When using the solution with corticosteroids and carbenoxolone due to the risk of sodium and water retention due to the sodium it contains, caution should be exercised.

Additional information regarding special populations No interaction studies have been conducted with TURKFLEKS 0.9% ISOTONIC SODIUM CHLORIDE on special populations. Pediatric population: No interaction studies have been conducted with TURKFLEKS 0.9% ISOTONIC SODIUM CHLORIDE on pediatric populations.

General advice Pregnancy

category: C Women of childbearing potential/Birth control (Contraception) TURKFLEKS %0.9 ISOTONIC SODIUM CHLORIDE has not been reported to have any effect on women of childbearing potential or any interaction with drugs used for birth control (contraception). Pregnancy There is no sufficient data on the use of isotonic sodium chloride solutions in pregnant women. Animal studies are insufficient regarding the effects on pregnancy / and-or / embryonal / fetal development / and-or / birth / and-or / postnatal development (see section 5.3). The potential risk for humans is unknown.

TURKFLEKS %0.9 İZOTONİK SODYUM KLORÜR yaşamsal önemi olan durumlar için gerekli olmadıkça gebelik döneminde kullanılmamalıdır. Sodyum klorür içeren çözeltilerle hayvan üreme çalışmaları gerçekleştirilmemiştir. TURKFLEKS %0.9 İZOTONİK SODYUM KLORÜR’ün gebe kadınlara uygulandığında fetusta hasara ya da üreme yeteneğinde bozulmaya yol açıp açmayacağı da bilinmemektedir. TURKFLEKS %0.9 İZOTONİK SODYUM KLORÜR, gebe kadınlarda ancak çok gerekliyse kullanılmalıdır.

Birth:

The effects of TURKFLEKS %0.9 ISOTONIC SODIUM CHLORIDE on the duration of labor and delivery, on forceps delivery or other interventions, or on other interventions that must be performed on the newborn, and on the subsequent growth, development, and functional maturation of the baby are not known when used during labor and delivery. It has been reported in the literature that solutions containing dextrose and sodium chloride have been used during labor and delivery. The fluid balance of the mother and fetus, glucose and electrolyte concentrations, and acid-base balance should be evaluated regularly or when the patient or fetus' condition requires it.

LACTATION

It is not known whether this drug passes into breast milk. Since it is known that many drugs pass into breast milk, TURKFLEKS 0.9% ISOTONIC SODIUM CHLORIDE should be used with caution in breastfeeding mothers.

FEMALES AND MALES OF REPRODUCTIVE POTENTIAL

There is no data on the effects of sodium chloride solutions on fertility.

OTHER SAFETY INFORMATION

Effects on use machines It is practically impossible to drive while using infusion solutions. There are no known effects on ability to drive and use machines after use.

ADVERSE REACTIONS

To report suspected adverse reactions" and "1-800-332-1088" (different telephone number for documents of type Vaccine Label (53404-0)

Under normal treatment conditions, no undesirable effects are expected. Undesirable effects may be due to a deficiency or excess of ions in the solution; therefore, sodium and chloride levels should be closely monitored. It is also necessary to be aware that additional drugs administered in diluted form may also cause adverse effects. In such a case, the product information of the additional drug administered should be consulted. Inadvertent application of intravenous sodium chloride therapy (e.g., in the postoperative period, in patients with heart or kidney failure) may lead to hypernatremia. Osmotically induced water movement may reduce intracellular volume, leading to dehydration of internal organs, especially the brain, and thrombosis and hemorrhage. When any addition is made to isotonic solutions that make the solution hypertonic, if the application is made subcutaneously, pain may occur at the injection site. When large volumes are administered, sodium accumulation, edema and hyperchloremic acidosis may occur. If an adverse reaction is observed during administration, the infusion should be stopped, the patient's condition should be evaluated and appropriate treatment measures should be taken.

Very common (≥ 1/10); common (≥ 1/100 to < 1/10); uncommon (≥ 1/1,000 to < 1/100); rare (≥ 1/10,000 to < 1/1,000); very rare (< 1/10,000), not known (cannot be estimated from available data)

The following adverse reactions are effects that may be seen as a result of excess sodium or chloride due to overdose or may develop depending on the application technique.

The frequency of these adverse reactions is unknown (they may be seen in too few patients to be determined with the available data). Blood and lymphatic system disorders Not known:Thrombosis; Hemorrhage. Metabolism and nutritional disorders Not known: Sodium retention; Water retention and edema; Aggravation of congestive heart failure (due to hypernatremia); Hyperchloremic acidosis. Nervous system disorders Not known: Headache, dizziness, restlessness, irritation, convulsions, coma and death (cerebral dehydration due to hypernatremia).

Cardiac disorders Not known: Tachycardia (due to hypernatremia). Vascular disorders Not known: Hypertension (due to hypernatremia). Respiratory, thoracic and mediastinal disorders Not known: Pulmonary edema, respiratory depression and respiratory arrest (due to hypernatremia). Gastrointestinal disorders Not known: Nausea, vomiting, diarrhea, abdominal cramps, thirst, decreased salivation (due to hypernatremia). Skin and subcutaneous tissue disorders Not known: Decreased sweating (due to hypernatremia). Musculoskeletal disorders, connective tissue and bone disorders Not known: Muscle twitching and stiffness (due to hypernatremia).

Kidney and urinary disorders Unknown: Renal failure (due to hypernatremia). General disorders and diseases related to the application site Unknown: Fever; Weakness (due to hypernatremia); Pain at the injection site (due to subcutaneous administration of a solution made hypertonic by adding it into it).

Surgical and medical procedures Unknown: Febrile reactions; Injection site infection; Venous thrombosis or phlebitis starting at the injection site and spreading; Extravasation and hypervolemia (adverse reactions that may be seen depending on the application technique). Reporting of suspected adverse reactions Reporting of suspected adverse reactions to drugs after authorization is of great importance. Reporting allows for continuous monitoring of the benefit/risk balance of the drug. Healthcare professionals should report any suspected adverse reactions to the Turkish Pharmacovigilance Center (TÜFAM) (www.titck.gov.tr; e-mail: tufam@titck.gov.tr; tel: 0 800 314 00 08; fax: 0 312 218 35 99).

DOSAGE AND ADMINISTRATION

Adverse reactions due to excess sodium in the body include nausea, vomiting, diarrhea, abdominal cramps, thirst, decreased saliva, tears and sweat, fever, tachycardia, hypertension, renal failure, peripheral and pulmonary edema, respiratory arrest, headache, dizziness, restlessness, irritation, weakness, muscle twitching and stiffness, convulsions, coma and death. Excessive chloride accumulation in the body can cause bicarbonate loss and a shift towards the acidic side in body fluids. If fluid or solute overload due to excessive infusion is observed during parenteral therapy, the patient should be re-evaluated and appropriate corrective treatments should be initiated.

Diuretics can be used to treat edema resulting from isotonic expansion, and an appropriate replacement therapy that will not cause fluid-electrolyte imbalance should be applied. Treatment of hypervolemic hypernatremia requires the removal of sodium from the body rather than water, and can be done by replacing diuretic-induced sodium and water loss with water alone. The main goal of treatment is to normalize the volume and composition of body fluids. If overdose is due to drugs added to the solution, the signs and symptoms of overdose depend on the properties of the added drug. If the dose is accidentally exceeded during treatment, the administration should be stopped, and the patient should be monitored for signs and symptoms related to the drug administered. Symptomatic and supportive treatments should be applied when necessary.

PHARMACODYNAMICS

Pharmacotherapeutic group: Intravenous solutions / Solutions affecting electrolyte balance ATC code: B05XA03 TURKFLEKS %0.9 ISOTONIC SODIUM CHLORIDE is an isotonic solution with an approximate osmolarity of 308 mOsm/l. When used for the maintenance of fluid and electrolyte balance, the pharmacodynamic properties of the solution consist of the properties of sodium and chloride in its composition. Ions such as sodium pass through the cell membrane using various transport mechanisms such as the sodium pump (Na-K-ATPase). Sodium plays an important role in nerve conduction, cardiac electrophysiology and renal metabolism. Chloride is primarily an extracellular anion. Intracellular chloride is found in high concentration in red blood cells and gastric mucosa. Chloride reabsorption follows sodium reabsorption. The pharmacodynamic properties of drugs added to the solution are the same as the pharmacodynamic properties of the added drug.

PHARMACOKINETICS

The pharmacokinetic properties of TURKFLEKS %0.9 ISOTONIC SODIUM CHLORIDE consist of the properties of its components (sodium and chloride). Absorption: Active substances in drugs administered intravenously reach their maximum plasma concentrations immediately after administration. Distribution: Sodium distribution varies according to the tissues: fast in muscle, liver, kidney, cartilage and skin, slow in erythrocytes and neurons, and very slow in bone. Chloride is mainly distributed in extracellular fluids. Biotransformation: The half-life after injection of radioactively labeled sodium (24Na) is 11-13 days for 99% of the injected sodium and one year for the remaining 1%.

Chloride closely follows sodium metabolism and changes in the body's acid-base balance are reflected by changes in chloride concentration. Elimination: Sodium is mainly excreted renally, but also the majority is reabsorbed renally. Small amounts of sodium are excreted in feces and sweat. Since chloride follows sodium metabolically, it is mainly excreted renally, and small amounts in feces and sweat. Linearity / non-linearity: When the electrolytes in the composition of TURKFLEKS 0.9% ISOTONIC SODIUM CHLORIDE are administered in the amount that will compensate for their deficiencies in the body, i.e. in therapeutic doses, it exhibits a linear pharmacokinetic behavior.

CLINICAL STUDIES

Preclinical safety data Since the components of the solution are physiological components of human and animal plasma and toxic effects are not expected in clinical application, studies have not been conducted with isotonic sodium chloride solutions to evaluate their carcinogenic, mutagenic potential and effects on fertility. The safety of drugs added to the solution should be considered separately.

PHARMACEUTICAL PROPERTIES

List of excipients: Water for injections

Incompatibilities

The compatibility of the drug to be added to the solution should be evaluated in advance. In cases where compatibility data are not available, no drug should be added to the solution. It is the responsibility of the physician performing the application to check whether the added drug is compatible by checking whether there is a color change and/or precipitation, insoluble compounds or crystallization after the drug is added. The compatibility of the drug to be added to TURKFLEKS %0.9 ISOTONIC SODIUM CHLORIDE should be decided by using the product information of the drug to be added. Before adding the drug to the solution, it should be confirmed that TURKFLEKS %0.9 ISOTONIC SODIUM CHLORIDE is soluble and stable at its pH.

TURKFLEKS %0.9 ISOTONIC SODIUM CHLORIDE should be used immediately after adding a compatible drug. Drugs known to be incompatible should not be added.

Shelf Life:

36 months.

Shelf life during use for drug dilution: From a microbiological point of view, it should be used immediately after preparation for application. In cases where it is not used immediately, the determination of the storage conditions and duration is the responsibility of the person who added/diluted the drug, and the duration is normally not longer than 24 hours at 2-8°C, unless this process is carried out under validated aseptic conditions.

Special precautions for storage

No special storage requirements, should be stored at room temperature below 30°C, in a place not exposed to direct light.

Nature and content of packaging 50, 100, 150, 250, 500, 1000 ml and 3000 ml PP (polypropylene) bags. The product has seven forms, with and without sets. Disposal of remaining substances from human medicinal products and other special precautions Unused products or waste materials should be disposed of in accordance with the ‘Medical Waste Control Regulation’ and the ‘Packaging and Packaging Waste Control Regulation’.

Directions for Use The solution should be checked before use.

The application is made intravenously with sterile apyrogen sets. Only clear, particle-free and intact packaging products should be used. The application should be started as soon as possible after the application set is attached to the product. To prevent air embolism that may occur due to residual air in the bag, serial connections should not be made with other infusion fluids. In cases where the air in the bag is not completely evacuated before application, applying pressure to intravenous solutions in flexible plastic bags to increase the flow rate may cause air embolism.

The solution should be administered using aseptic technique via a sterile administration set.

In order to prevent air from entering the system, the administration set should be flushed with liquid before use. Additional drugs can be added to the injection tip using a needle under aseptic conditions before and during infusion. The isotonicity of the final product should be determined before parenteral administration. The drug added to the patient must be completely mixed with the solution before administration. Solutions containing additional drugs should be used immediately after adding the drug; they should not be stored for later use. Addition of additional drugs to the solution or incorrect administration technique may cause a fever reaction due to pyrogen contamination of the product. In the event of an adverse reaction, the infusion should be stopped immediately. For single use.

Partially used solutions should not be stored. Partially used bags should not be reconnected to patient-administered systems.

To open:

1. Check the integrity of the outer packaging and check for leaks; do not use if the packaging is damaged.

2. Tear open the protective outer packaging.

3. Check that the bag inside the protective packaging is intact by squeezing it. Check that the solution inside the bag is clear and does not contain foreign matter.

Preparations for application:

1. Hang the bag.

2. Remove the protective cap from the application tip.

3. Firmly insert the spike of the application set into the application tip.

4. The instructions for use of the set must be followed for the application of the solution to the patient. Addition of additional drugs: Caution: As with all parenteral solutions, all substances to be added to the product must be compatible with the product. If additions are to be made to the product, compatibility must be checked in the final mixture before administration to the patient.

Adding medication before application

1. Disinfect the drug application tip.

2. The drug to be added is added to the bag with a syringe with a 19-22 gauge needle.

3. The solution and the drug added are mixed thoroughly. In concentrated drugs such as potassium chloride, the application outlet of the bag is gently tapped while in the upright position to mix.

Attention: Bags with additional drugs applied should not be stored. Adding medication during application

1. The clamp of the set is closed.

2. Disinfect the drug application tip.

3. The drug to be added is applied from the drug application tip with a syringe with a 19-22 gauge needle.

4. Remove from the solution hanger and turn upside down.

5. In this position, the application outlet and injection inlet of the bag are gently tapped to mix the solution and additional drug.

6. Return the bag to its original position, open the clamp and continue the application.
LICENSE HOLDER Turk İlaç ve Serum Sanayi A.Ş. Bugduz Mah. Enver Pasa Cad. No: 8 06750 Akyurt / Ankara Phone: (0312) 837 67 67 Fax: (0312) 837 66 77 E-mail: info@turkilac.com.tr 8. LICENSE NUMBER 2015 / 160 9. FIRST LICENSE DATE / LICENSE RENEWAL DATE First license date: 16.02.2015

HEALTH CARE PROVIDER LETTER

Turkfleks % 0,9 SODIUM CHLORIDE INJECTION, SOLUTION
Turk Ilac Ve Serum Sanayi

Disclaimer: This drug has not been found by FDA to be safe and effective, and this labeling has not been approved by FDA.

For further information please click the link below.

http://www.fda.gov/Drugs/GuidanceComplianceRegulatoryInformation/EnforcementActivitiesbyFDA/SelectedEnforcementActionsonUnapprovedDrugs/default.htm

Active substance: Each 100 ml solution contains 0.9 g sodium chloride.

Excipients: Water

The osmolarity of the solution is 308 mOsmol/l.

Ion concentrations of the solution:

- sodium: 154 mEq/L

- chloride: 154 mEq/L

PHARMACEUTICAL FORM

Sterile solution for intravenous infusion

Therapeutic indications

TURKFLEKS %0.9 ISOTONIC SODIUM CHLORIDE is a source of water for electrolytes and in addition the following cases:

- In the treatment of isotonic extracellular dehydration

- In the treatment of sodium losses

- As a diluent solution for drugs with which it is compatible in parenteral applications

Dosage / frequency and duration of application:

The dose to be applied should be determined by the physician for each patient based on the patient's age, body weight, clinical condition, and especially the patient's hydration status. Serum electrolyte concentrations should be carefully monitored during treatment.

In general, in the treatment of isotonic extracellular dehydration and sodium losses, unless otherwise recommended by the physician, it is recommended at a dose of 500 - 3000 ml per 24 hours for adults, adolescents and the elderly, and 20 - 100 ml/kg per 24 hours for infants and children. 2 / 13 When used as a drug diluent, the dose should be determined according to the nature of the drug being diluted and the dosage schedule. In general, 50 - 250 ml of liquid is sufficient. The frequency of application and dose are adjusted by the physician according to the clinical condition of the patient.

The recommended TURKFLEKS %0.9 ISOTONIC SODIUM CHLORIDE infusion rate when used as a diluent is adjusted according to the recommended dose of the diluted drug.

Application method:

Application is made intravenously through peripheral or central veins with sterile apyrogen sets.

Contraindications:

The solution is contraindicated in patients with hypernatremia or hyperchloremia. It should also not be used in cases where sodium or chloride administration would be clinically detrimental.

Instructions For Use:

Partially used solutions should not be stored. Partially used bags should not be reconnected to patient-administered systems.

To open:

1. Check the integrity of the outer packaging and check for leaks; do not use if the packaging is damaged.

2. Tear open the protective outer packaging. 7 / 7

3. Check that the bag inside the protective packaging is intact by squeezing it.

Check that the solution in the bag is clear and does not contain foreign matter. Preparations for application:

1. Hang the bag.

2. Remove the protective cap from the application tip.

3. Firmly insert the spike of the application set into the application tip.

4. The instructions for use of the set must be followed for the application of the solution to the patient.

Adding additional drugs:

Caution: As with all parenteral solutions, all substances to be added to the product must be compatible with the product. If the product is to be added, compatibility should be checked in the final mixture before administering to the patient.

Adding drugs before application

1. Disinfect the drug application tip.

2. The drug to be added is added to the bag from the drug application tip with a syringe with a 19-22 gauge needle.

3. Mix the solution and the drug added thoroughly. In dense drugs such as potassium chloride, the application outlet of the bag is gently tapped while in the up position to ensure mixing.

Caution: Bags with additional drugs applied should not be stored.

Adding drugs during application

1. Close the clamp of the set.

2. Disinfect the drug application tip.

3. The drug to be added is added to the bag from the drug application tip with a syringe with a 19-22 gauge needle.

4. Remove from the solution hanger and turn upside down.

5. In this position, the application outlet and injection inlet of the bag are gently tapped to ensure that the solution and additional medication are mixed.

6. Return the bag to its original position, open the clamp and continue the application.

3/30/

March 30, 2025

Subject: Temporary importation of 0.9% Sodium Chloride Injection from Turk Ilac located in Ankara-TURKEY to address drug shortages per https://dps.fda.gov/drugshortages/activeingredient/sodium-chloride-09--injection

To prevent a shortage of large volume parenteral fluid drug products, Turk Ilac ve Serum Sanayi is coordinating with the U.S. Food and Drug Administration (FDA) to temporarily import 0.9% Sodium Chloride Injection (50ml, 100ml, 150ml, 250ml, 500ml, 1000 ml, and 3000ml) from Turk Ilac ve Serum Sanayi manufacturing facility located in Ankara/TURKEY. FDA has not approved these products manufactured by Turk Ilac ve Serum Sanayi.

Effective immediately, and during this temporary period, Turk Ilac ve Serum Sanayi will offer the following imported product from Turk Ilac ve Serum Sanayi facility located in Ankara/TURKEY:

Product Name and Description | Volume | Bags per Box | NDC Code
Turkfleks %0.9 Sodium Chloride | 50ml | 100 | 85160-200-10
Turkfleks %0.9 Sodium Chloride | 100ml | 50 | 85160-200-20
Turkfleks %0.9 Sodium Chloride | 150ml | 50 | 85160-200-30
Turkfleks %0.9 Sodium Chloride | 250ml | 25 | 85160-200-40
Turkfleks %0.9 Sodium Chloride | 500ml | 20 | 85160-200-50
Turkfleks %0.9 Sodium Chloride | 1000ml | 20 | 85160-200-60
Turkfleks %0.9 Sodium Chloride | 3000ml | 10 | 85160-200-70

Please note the following:

- Upon receiving Submission Acceptance Turk Ilac ve Serum Sanayi will have bag labels written in both Turkish and English.
- The bag labels will contain the active pharmaceutical ingredient, concentration, volume, and NDC code in English.
- The imported products' administration port system is fully compatible with sets marketed in the United States.
- The imported products use a carton box that is taped closed. To avoid damage to the solution container, take care not to use sharp instruments to open the box.
- The imported products do not contain barcodes on the unit label. Alternative procedures should be followed to ensure that the correct drug product is being used in all systems and processes and administered to individual patients. For example, institutions should consider manually inputting the product into their systems and confirm that barcode systems do not provide incorrect information when the product is scanned.
- 0.9% Sodium Chloride Injection is available only by prescription in the United States. However, the imported products do not have the statement "Rx only" on the labeling.
- USE A NEW BAG IF PARTICULATES ARE VISIBLE OR IF THE IV BAG CONTAINS A LEAK.

Additional key differences in the labeling between the FDA-approved product and the imported products are stated in the product comparison table at the end of this letter as follows:

Table 1. Key differences between FDA-approved and Turkfleks 0.9% Sodium Chloride Injection

Table 2. Label images of FDA-approved and Turkfleks 0.9% Sodium Chloride Injection

Reporting Adverse Events or Product Quality Issues

To report adverse events associated with these imported products, please use the contact us at info@turkilac.com.tr.

Adverse events or quality problems experienced with the use of these imported products may also be reported to the FDA's MedWatch Adverse Event Reporting program either online, by regular mail or by fax:

- Complete and submit the report Online: www.fda.gov/medwatch/report.htm
- Regular mail or Fax: Download form www.fda.gov/MedWatch/getforms.htm

or call 1-800332-1088 to request a reporting form, then complete and return to the address on the preaddressed form or submit by fax to 1-800-FDA-0178 (1-800-332-0178).

Sincerely,

Mehmet Berat Battal

Table 1: Key Differences between FDA Approved product and Turkfleks %0.9 Sodium Chloride

 | FDA- Approved Product | Turkfleks Import from Turkey
Product Name | 0.9% Sodium Chloride injection USP | %0.9 Sodium Chloride Injection
Label Volume | 50 mL, 100 mL, 150 mL, 250 mL, 500 mL, 1000 mL | 50 mL, 100 mL, 150 mL, 250 mL, 500 mL, 1000 mL, 3000 mL
Language of the Labels | English | Turkish*
Indications | Sodium Chloride Injection, USP is indicated as a source of water and electrolytes. 0.9% Sodium Chloride. Injection, USP is also indicated for use as a priming solution in hemodialysis procedures. | Source of water for electrolytes and:; - In the treatment of isotonic extracellular dehydration; - In the treatment of sodium losses; - As a diluent solution for drugs with which it is compatible in parenteral applications
Active Ingredients | Each 100 ml contains 900 mg Sodium Chloride, USP | Each 100 ml contains 9g Sodium Chloride
Additional Information | pH is 5.0 (4.5-7.0) Osmolarity 308 mOsm/L (calc) | pH is 5.5 (4.5-7.0) Osmolarity mOsm/L (calc)
Store Conditions | Store at room temperature 25C/77F | Store at below 30C
Container Type | Viaflex PVC | Polypropylene

*Upon receiving Submission Acceptance Turk Ilac ve Serum Sanayi will have bag labels written in both Turkish and English.

Table 2: Label Images of FDA-approved and Turkfleks %0.9 Sodium Chloride Injection